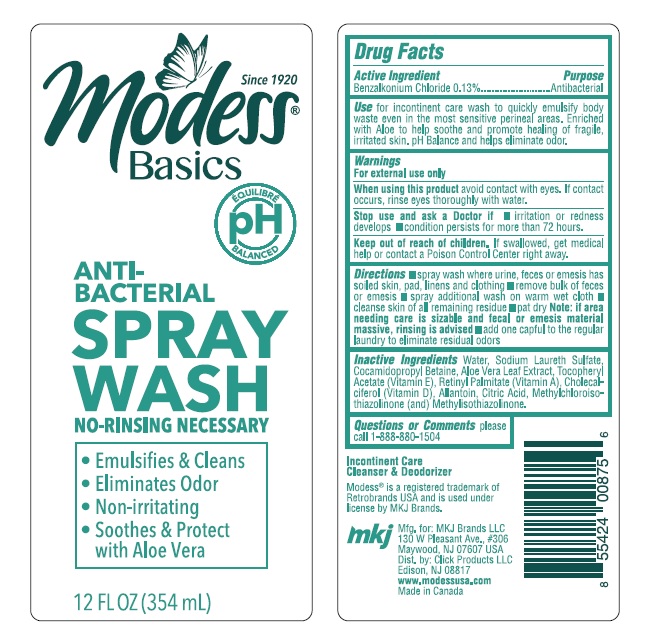 DRUG LABEL: Benzalkonium Chloride
NDC: 71611-080 | Form: LIQUID
Manufacturer: Click Products LLC
Category: otc | Type: HUMAN OTC DRUG LABEL
Date: 20210825

ACTIVE INGREDIENTS: BENZALKONIUM CHLORIDE 1.3 mg/1 mL
INACTIVE INGREDIENTS: WATER; CITRIC ACID ACETATE; CHOLECALCIFEROL; ALLANTOIN; POLYQUATERNIUM-10 (1000 MPA.S AT 2%); SODIUM LAURETH SULFATE; METHYLCHLOROISOTHIAZOLINONE; METHYLISOTHIAZOLINONE; ALOE VERA LEAF; .ALPHA.-TOCOPHEROL ACETATE; COCAMIDOPROPYL BETAINE; VITAMIN A PALMITATE

Modess Basics Antibacterial spray wash

ACTIVE INGREDIENT

Benzalkonium Chloride - 0.13%

Purpose - Antibacterial

INDICATIONS AND USAGE

for incontinent care wash to quickly emulsify body waste even in the most sensitive perineal areas. Enriched with Aloe to help soothe and promote healing of fragile irritated skin. pH balance and helps eliminate odor

WARNINGS

Warning - For external use only

When using this product avoid contact with eyes. If contact occurs, rinse eyes thoroughly with water

Stop use and ask a doctor if

- irritaion or redness develops
- condition persists for more than 72 hours

Keep out of reach of children. If swallowed, get medical help or contact a Poison Control Center right away

DOSAGE AND ADMINISTRATION

Spray wash where urine, feces or emesis has soiled skin, pad, linens, and clothing. Remove bulk of feces or emesis.

Spray additional wash on a warm wet cloth.

cleanse the skin of all remaining residue

Note: If the area needing care is sizable and fecal or emesis material massive- rinsing is advised.

add one capful to the regular laundry to eliminate residual odors.

INACTIVE INGREDIENT

Water, Sodium Laureth Sulfate, Cocamidopropyl betaine, aloe vera leaf, Vit E, Vit D, Vit A, Allantoin, Citric acid, Methylchloroisothiazolinone and Methylisothiazolinone